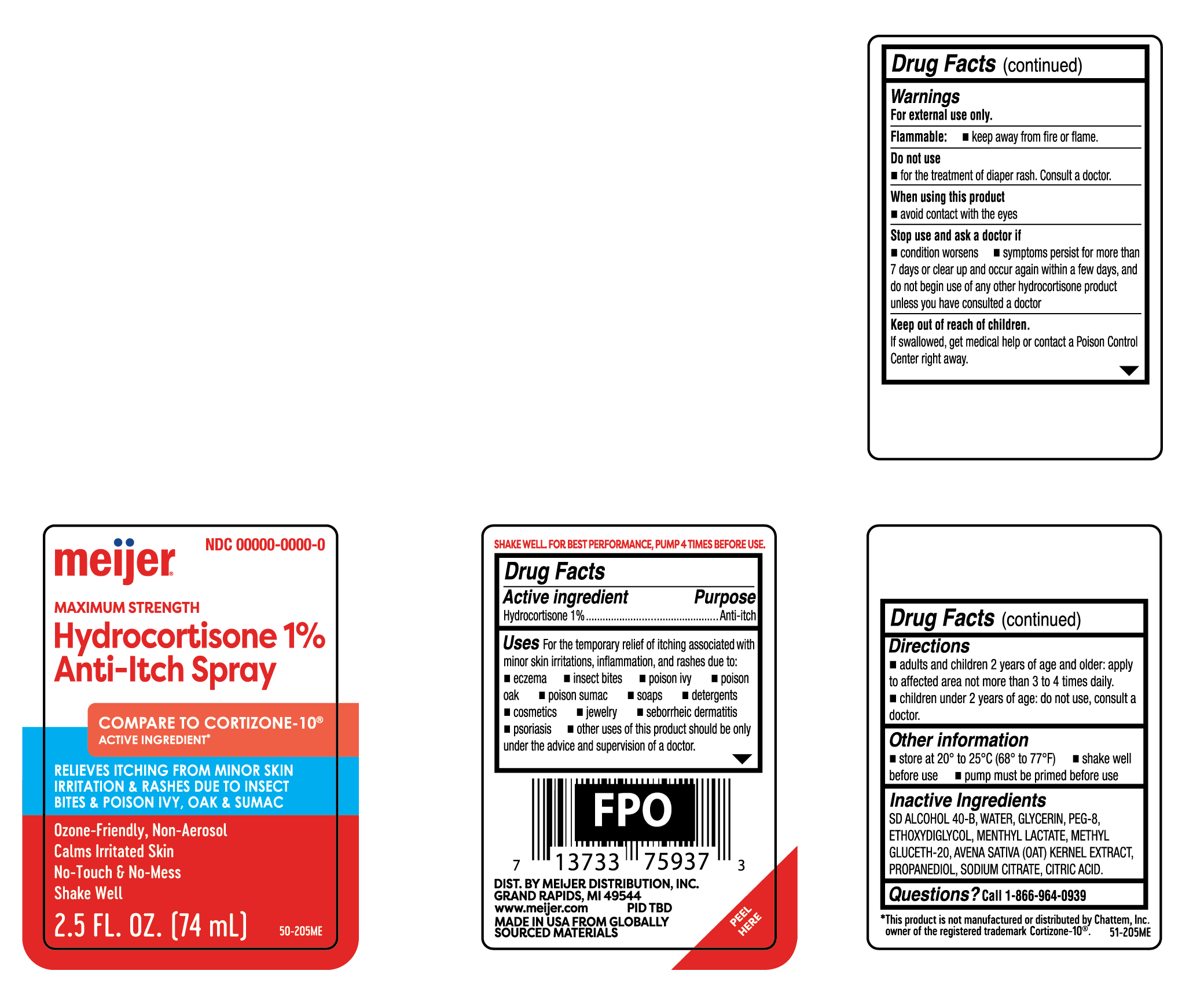 DRUG LABEL: Hydrocortisone
NDC: 79481-9967 | Form: SPRAY
Manufacturer: Meijer Distribution Inc.
Category: otc | Type: HUMAN OTC DRUG LABEL
Date: 20251030

ACTIVE INGREDIENTS: HYDROCORTISONE 10 mg/1 mL
INACTIVE INGREDIENTS: ALCOHOL; WATER; GLYCERIN; POLYETHYLENE GLYCOL 400; DIETHYLENE GLYCOL MONOETHYL ETHER; MENTHYL LACTATE; METHYL GLUCETH-20; OAT; PROPANEDIOL; SODIUM CITRATE; CITRIC ACID

Meijer Hydrocortisone 1% Anti-Itch Spray

Active ingredient

Hydrocortisone 1%

Purpose

Anti-itch

Uses

for the temporary relief of itching associated with minor skin irritations, inflammation, and rashes due to:

- eczema
- insect bites
- poison ivy
- poison oak
- poison sumac
- soaps
- detergents
- cosmetics
- jewelry
- seborrheic dermatitis
- psoriasis
- other uses of this product should be only under the advice and supervision of a doctor

Warnings

For external use only.

Flammable:

Keep away from fire or flame.

Do not use

- for the treatment of diaper rash. Consult a doctor.

When using this product

- avoid contact with the eyes

Stop use and ask a doctor if

- condition worsens
- symptoms persist for more than 7 days or clear up and occur again within a few days, and do not begin use of any other hydrocortisone product unless you have consulted a doctor

Keep out of the reach of children.

If swallowed, get medical help or contact a Poison Control Center right away.

Directions

- adults and children 2 years of age and older: spray affected area not more than 3 to 4 times daily
- children under 2 years of age: do not use, consult a doctor

Other Information

- store at 20o to 25oC (68o to 77oF)
- shake well before use
- pump must be primed before use

Inactive ingredients

SD ALCOHOL 40-B, WATER, GLYCERIN, PEG-8, ETHOXYDIGLYCOL, MENTHYL LACTATE, METHYL GLUCETH-20, AVENA SATIVA (OAT) KERNEL EXTRACT, PROPANEDIOL, SODIUM CITRATE, CITRIC ACID.

Questions ?

Call 1-866-964-0939

Principal Display Panel

MAXIMUM STRENGTH

Hydrocortisone 1%/

Anti-Itch Spray

COMPARE TO CORTIZONE-10

ACTIVE INGREDIENT

RELIEVES ITCHING FROM MINOR SKIN

IRRITATION & RASHES DUE TO INSECT

BITES & POSION IVY, OAK & SUMAC

Ozone-Friendly, Non-Aerosol

Calms Irritated Skin

No-Touch & No-Mess

Shake Well

2.5 FL. 0Z. (74 mL)

meijer